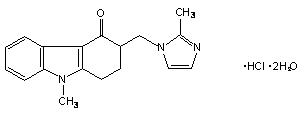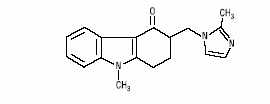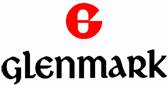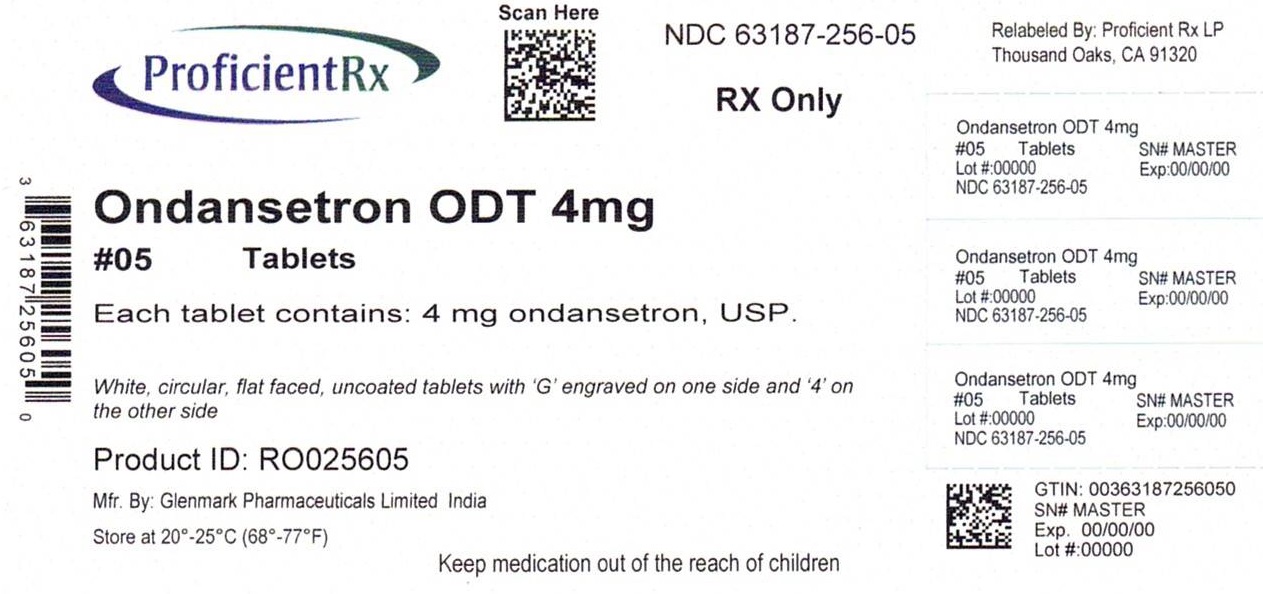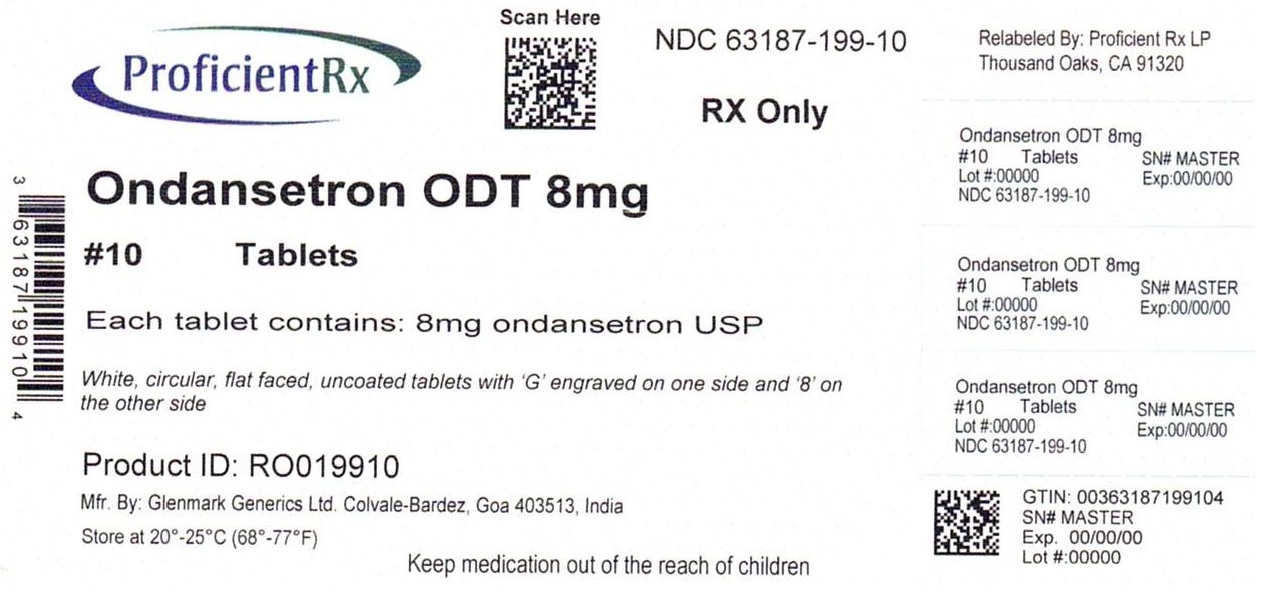 DRUG LABEL: Ondansetron
NDC: 63187-256 | Form: TABLET, ORALLY DISINTEGRATING
Manufacturer: Proficient Rx LP
Category: prescription | Type: HUMAN PRESCRIPTION DRUG LABEL
Date: 20251101

ACTIVE INGREDIENTS: ONDANSETRON 4 mg/1 1
INACTIVE INGREDIENTS: ASPARTAME; SILICON DIOXIDE; CROSPOVIDONE (120 .MU.M); MAGNESIUM STEARATE; MANNITOL; SODIUM STEARYL FUMARATE

Ondansetron Tablets USP, for oral use
Ondansetron Orally Disintegrating Tablets USP, for oral use

DESCRIPTION

The active ingredient in ondansetron tablets USP is ondansetron hydrochloride (HCl) USP as the dihydrate, the racemic form of ondansetron and a selective blocking agent of the serotonin 5-HT3 receptor type. Chemically it is (±) 1, 2, 3, 9-tetrahydro-9-methyl-3-[(2-methyl-1H-imidazol-1-yl)methyl]-4H-carbazol-4-one, monohydrochloride, dihydrate. It has the following structural formula:

The empirical formula is C18H19N3O•HCl•2H2O, representing a molecular weight of 365.85.

Ondansetron HCl USP dihydrate is a white to off-white powder that is sparingly soluble in water and in alcohol; soluble in methanol, slightly soluble in isopropyl alcohol, and in dichloromethane; very slightly soluble in acetone, in chloroform and in ethyl acetate.

The active ingredient in ondansetron orally disintegrating tablets USP is ondansetron base, the racemic form of ondansetron, and a selective blocking agent of the serotonin 5-HT3 receptor type. Chemically it is (±) 1, 2, 3, 9-tetrahydro-9-methyl-3-[(2-methyl-1H-imidazol-1-yl)methyl]-4H-carbazol-4-one. It has the following structural formula:

The empirical formula is C18H19N3O representing a molecular weight of 293.4.

Each 4-mg ondansetron tablet USP for oral administration contains ondansetron HCl USP dihydrate equivalent to 4 mg of ondansetron. Each 8-mg ondansetron tablet USP for oral administration contains ondansetron HCl USP dihydrate equivalent to 8 mg of ondansetron. Each 24-mg ondansetron tablet USP for oral administration contains ondansetron HCl USP dihydrate equivalent to 24 mg of ondansetron. Each tablet also contains the inactive ingredients colloidal silicon dioxide, hypromellose, iron oxide yellow (8 mg tablet only), iron oxide red (24 mg tablet only), lactose monohydrate, magnesium stearate, microcrystalline cellulose, pregelatinized starch, titanium dioxide and triacetin.

Each 4-mg ondansetron orally disintegrating tablet USP for oral administration contains 4 mg ondansetron base. Each 8-mg ondansetron orally disintegrating tablet USP for oral administration contains 8 mg ondansetron base. Each ondansetron orally disintegrating tablet USP also contains the inactive ingredients aspartame, colloidal silicon dioxide, crospovidone, magnesium stearate, mannitol, sodium stearyl fumarate and strawberry flavor. Ondansetron orally disintegrating tablets USP are an orally administered formulation of ondansetron which rapidly disintegrates on the tongue and does not require water to aid dissolution or swallowing. This product disintegrates in approximately 60 seconds.

CLINICAL PHARMACOLOGY

Pharmacodynamics:

Ondansetron is a selective 5-HT3 receptor antagonist. While its mechanism of action has not been fully characterized, ondansetron is not a dopamine-receptor antagonist. Serotonin receptors of the 5-HT3 type are present both peripherally on vagal nerve terminals and centrally in the chemoreceptor trigger zone of the area postrema. It is not certain whether ondansetron's antiemetic action is mediated centrally, peripherally, or in both sites. However, cytotoxic chemotherapy appears to be associated with release of serotonin from the enterochromaffin cells of the small intestine. In humans, urinary 5-HIAA (5-hydroxyindoleacetic acid) excretion increases after cisplatin administration in parallel with the onset of emesis. The released serotonin may stimulate the vagal afferents through the 5-HT3 receptors and initiate the vomiting reflex.

In animals, the emetic response to cisplatin can be prevented by pretreatment with an inhibitor of serotonin synthesis, bilateral abdominal vagotomy and greater splanchnic nerve section, or pretreatment with a serotonin 5-HT3 receptor antagonist.

In normal volunteers, single intravenous doses of 0.15 mg/kg of ondansetron had no effect on esophageal motility, gastric motility, lower esophageal sphincter pressure, or small intestinal transit time. Multiday administration of ondansetron has been shown to slow colonic transit in normal volunteers. Ondansetron has no effect on plasma prolactin concentrations.

Ondansetron does not alter the respiratory depressant effects produced by alfentanil or the degree of neuromuscular blockade produced by atracurium. Interactions with general or local anesthetics have not been studied.

Pharmacokinetics:

Ondansetron is well absorbed from the gastrointestinal tract and undergoes some first-pass metabolism. Mean bioavailability in healthy subjects, following administration of a single 8-mg tablet, is approximately 56%.

Ondansetron systemic exposure does not increase proportionately to dose. AUC from a 16-mg tablet was 24% greater than predicted from an 8-mg tablet dose. This may reflect some reduction of first-pass metabolism at higher oral doses. Bioavailability is also slightly enhanced by the presence of food but unaffected by antacids.

Ondansetron is extensively metabolized in humans, with approximately 5% of a radiolabeled dose recovered as the parent compound from the urine. The primary metabolic pathway is hydroxylation on the indole ring followed by subsequent glucuronide or sulfate conjugation. Although some nonconjugated metabolites have pharmacologic activity, these are not found in plasma at concentrations likely to significantly contribute to the biological activity of ondansetron.

In vitro metabolism studies have shown that ondansetron is a substrate for human hepatic cytochrome P-450 enzymes, including CYP1A2, CYP2D6, and CYP3A4. In terms of overall ondansetron turnover, CYP3A4 played the predominant role. Because of the multiplicity of metabolic enzymes capable of metabolizing ondansetron, it is likely that inhibition or loss of one enzyme (e.g., CYP2D6 genetic deficiency) will be compensated by others and may result in little change in overall rates of ondansetron elimination. Ondansetron elimination may be affected by cytochrome P-450 inducers. In a pharmacokinetic study of 16 epileptic patients maintained chronically on CYP3A4 inducers, carbamazepine, or phenytoin, reduction in AUC, Cmax, and T½ of ondansetron was observed.^1 This resulted in a significant increase in clearance. However, on the basis of available data, no dosage adjustment for ondansetron is recommended (see PRECAUTIONS: Drug Interactions).

In humans, carmustine, etoposide, and cisplatin do not affect the pharmacokinetics of ondansetron.

Gender differences were shown in the disposition of ondansetron given as a single dose. The extent and rate of ondansetron's absorption is greater in women than men. Slower clearance in women, a smaller apparent volume of distribution (adjusted for weight), and higher absolute bioavailability resulted in higher plasma ondansetron levels. These higher plasma levels may in part be explained by differences in body weight between men and women. It is not known whether these gender-related differences were clinically important. More detailed pharmacokinetic information is contained in Tables 1 and 2 taken from 2 studies.

Table 1. Pharmacokinetics in Normal Volunteers: Single 8-mg Ondansetron Tablet Dose

Age-group (years) | Mean Weight (kg) | n | Peak Plasma Concentration (ng/mL) | Time of Peak Plasma Concentration (h) | Mean Elimination Half-life (h) | Systemic Plasma Clearance L/h/kg | Absolute Bioavailability
18-40 M; F | 69; 62.7 | 65 | 26.2; 42.7 | 2; 1.7 | 3.1; 3.5 | 0.403 0.354 | 0.483 0.663
61-74 M; F | 77.5 60.2 | 66 | 24.1; 52.4 | 2.1; 1.9 | 4.1; 4.9 | 0.384 0.255 | 0.585 0.643
≥ 75 M F | 78 67.6 | 56 | 37; 46.1 | 2.2; 2.1 | 4.5; 6.2 | 0.277 0.249 | 0.619 0.747

Table 2. Pharmacokinetics in Normal Volunteers: Single 24-mg Ondansetron Tablet Dose

Age-group; (years) | Mean; Weight; (kg) | n | Peak Plasma; Concentration; (ng/mL) | Time of; Peak Plasma; Concentration; (h) | Mean; Elimination; Half-life; (h)
18-43 M; F | 84.1; 71.8 | 8; 8 | 125.8; 194.4 | 1.9; 1.6 | 4.7; 5.8

A reduction in clearance and increase in elimination half-life are seen in patients over 75 years of age. In clinical trials with cancer patients, safety and efficacy were similar in patients over 65 years of age and those under 65 years of age; there was an insufficient number of patients over 75 years of age to permit conclusions in that age-group. No dosage adjustment is recommended in the elderly.

In patients with mild-to-moderate hepatic impairment, clearance is reduced 2-fold and mean half-life is increased to 11.6 hours compared to 5.7 hours in normals. In patients with severe hepatic impairment (Child-Pugh^2 score of 10 or greater), clearance is reduced 2-fold to 3-fold and apparent volume of distribution is increased with a resultant increase in half-life to 20 hours. In patients with severe hepatic impairment, a total daily dose of 8 mg should not be exceeded.

Due to the very small contribution (5%) of renal clearance to the overall clearance, renal impairment was not expected to significantly influence the total clearance of ondansetron. However, ondansetron oral mean plasma clearance was reduced by about 50% in patients with severe renal impairment (creatinine clearance <30 mL/min). This reduction in clearance is variable and was not consistent with an increase in half-life. No reduction in dose or dosing frequency in these patients is warranted.

Plasma protein binding of ondansetron as measured in vitro was 70% to 76% over the concentration range of 10 to 500 ng/mL. Circulating drug also distributes into erythrocytes.

Four-and 8-mg doses of ondansetron orally disintegrating tablets are bioequivalent to corresponding doses of ondansetron tablets and may be used interchangeably. One 24-mg ondansetron tablet is bioequivalent to and interchangeable with three 8-mg ondansetron tablets.

CLINICAL TRIALS

Chemotherapy-Induced Nausea and Vomiting:

Highly Emetogenic Chemotherapy:

In 2 randomized, double-blind, monotherapy trials, a single 24-mg ondansetron tablet was superior to a relevant historical placebo control in the prevention of nausea and vomitingassociated with highly emetogenic cancer chemotherapy,including cisplatin ≥50 mg/m^2. Steroid administration was excluded from these clinical trials. More than 90% of patients receiving a cisplatin dose ≥50 mg/m^2 in thehistorical placebo comparator experienced vomiting in the absence of antiemetic therapy.

The first trial compared oral doses of ondansetron 24 mg once a day, 8 mg twice a day, and 32 mg once a day in 357 adult cancer patients receiving chemotherapy regimens containing cisplatin ≥50 mg/m^2. A total of 66% of patients in the ondansetron 24-mg once- a-day group, 55% in the ondansetron 8-mg twice-a-day group, and 55% in the ondansetron 32-mg once-a-day group completed the 24-hour study period with 0 emetic episodes and no rescue antiemetic medications, the primary endpoint of efficacy. Each of the 3 treatment groups was shown to be statistically significantly superior to a historical placebo control.

In the same trial, 56% of patients receiving oral ondansetron 24 mg once a day experienced no nausea during the 24-hour study period, compared with 36% of patients in the oral ondansetron 8-mg twice-a-day group (P = 0.001) and 50% in the oral ondansetron 32-mg once-a-day group.

In a second trial, efficacy of the oral ondansetron 24-mg once-a-day regimen in the prevention of nausea and vomiting associated with highly emetogenic cancer chemotherapy, including cisplatin ≥50 mg/m^2, was confirmed.

Moderately Emetogenic Chemotherapy:

In 1 double-blind US study in 67 patients, ondansetron tablets 8 mg administered twice a day were significantly more effective than placebo in preventing vomiting induced by cyclophosphamide-based chemotherapy containing doxorubicin. Treatment response is based on the total number of emetic episodes over the 3-day study period. The results of this study are summarized in Table 3:

Table 3. Emetic Episodes: Treatment Response

 | Ondansetron 8-mg b.i.d. ondansetron tablets* | Placebo | P Value
Number of patients | 33 | 34
Treatment response; 0 Emetic episodes; 1-2 Emetic episodes More than 2 emetic episodes/withdrawn | 20 (61%); 6 (18%); 7 (21%) | 2 (6%); 8 (24%); 24 (71%) | < 0.001; < 0.001
Median number of emetic episodes | 0 | Undefined†
Median time to first emetic episode (h) | Undefined‡ | 6.5

* The first dose was administered 30 minutes before the start of emetogenic chemotherapy, with a subsequent dose 8 hours after the first dose. An 8 mg ondansetron tablet was administered twice a day for 2 days after completion of chemotherapy.

† Median undefined since at least 50% of the patients were withdrawn or had more than 2 emetic episodes.

‡ Median undefined since at least 50% of patients did not have any emetic episodes.

In 1 double-blind US study in 336 patients, ondansetron tablets 8 mg administered twice a day were as effective as ondansetron tablets 8 mg administered 3 times a day in preventing nausea and vomiting induced by cyclophosphamide-based chemotherapy containing either methotrexate or doxorubicin. Treatment response is based on the total number of emetic episodes over the 3-day study period. The results of this study are summarized in Table 4:

Table 4. Emetic Episodes: Treatment Response

Ondansetron
 | 8-mg b.i.d.; ondansetron tablets* | 8-mg t.i.d.; ondansetron tablets†
Number of patients | 165 | 171
Treatment response; 0 Emetic episodes; 1-2 Emetic episodes; More than 2 emetic episodes/withdrawn | 101 (61%); 16 (10%); 48 (29%) | 99 (58%); 17 (10%); 55 (32%)
Median number of emetic episodes | 0 | 0
Median time to first emetic episode (h) | Undefined‡ | Undefined‡
Median nausea scores (0-100)§ | 6 | 6

* The first dose was administered 30 minutes before the start of emetogenic chemotherapy, with a subsequent dose 8 hours after the first dose. An 8-mg ondansetron tablet was administered twice a day for 2 days after completion of chemotherapy.

† The first dose was administered 30 minutes before the start of emetogenic chemotherapy, with subsequent doses 4 and 8 hours after the first dose. An 8-mg ondansetron tablet was administered 3 times a day for 2 days after completion of chemotherapy.

‡ Median undefined since at least 50% of patients did not have any emetic episodes.

§ Visual analog scale assessment: 0 = no nausea, 100 = nausea as bad as it can be.

Re-treatment:

In uncontrolled trials, 148 patients receiving cyclophosphamide-based chemotherapy were re-treated with ondansetron tablets 8 mg 3 times daily during subsequent chemotherapy for a total of 396 re-treatment courses. No emetic episodes occurred in 314 (79%) of the re-treatment courses, and only 1 to 2 emetic episodes occurred in 43 (11%) of the re-treatment courses.

Pediatric Studies:

Three open-label, uncontrolled, foreign trials have been performed with 182 pediatric patients 4 to 18 years old with cancer who were given a variety of cisplatin or noncisplatin regimens. In these foreign trials, the initial dose of ondansetron hydrochloride injection ranged from 0.04 to 0.87 mg/kg for a total dose of 2.16 to 12 mg. This was followed by the administration of ondansetron tablets ranging from 4 to 24 mg daily for 3 days. In these studies, 58% of the 170 evaluable patients had a complete response (no emetic episodes) on day 1. Two studies showed the response rates for patients less than 12 years of age who received ondansetron tablets 4 mg 3 times a day to be similar to those in patients 12 to 18 years of age who received ondansetron tablets 8 mg 3 times daily. Thus, prevention of emesis in these pediatric patients was essentially the same as for patients older than 18 years of age. Overall, ondansetron tablets were well tolerated in these pediatric patients.

Radiation-Induced Nausea and Vomiting:

Total Body Irradiation:

In a randomized, double-blind study in 20 patients, ondansetron tablets (8 mg given 1.5 hours before each fraction of radiotherapy for 4 days) were significantly more effective than placebo in preventing vomiting induced by total body irradiation. Total body irradiation consisted of 11 fractions (120 cGy per fraction) over 4 days for a total of 1,320 cGy. Patients received 3 fractions for 3 days, then 2 fractions on day 4.

Single High-Dose Fraction Radiotherapy:

Ondansetron was significantly more effective than metoclopramide with respect to complete control of emesis (0 emetic episodes) in a double-blind trial in 105 patients receiving single high-dose radiotherapy (800 to 1,000 cGy) over an anterior or posterior field size of ≥80 cm^2 to the abdomen. Patients received the first dose of ondansetron tablets (8 mg) or metoclopramide (10 mg) 1 to 2 hours before radiotherapy. If radiotherapy was given in the morning, 2 additional doses of study treatment were given (1 tablet late afternoon and 1 tablet before bedtime). If radiotherapy was given in the afternoon, patients took only 1 further tablet that day before bedtime. Patients continued the oral medication on a 3 times a day basis for 3 days.

Daily Fractionated Radiotherapy:

Ondansetron was significantly more effective than prochlorperazine with respect to complete control of emesis (0 emetic episodes) in a double-blind trial in 135 patients receiving a 1- to 4-week course of fractionated radiotherapy (180 cGy doses) over a field size of ≥100 cm^2 to the abdomen. Patients received the first dose of ondansetron tablets (8 mg) or prochlorperazine (10 mg) 1 to 2 hours before the patient received the first daily radiotherapy fraction, with 2 subsequent doses on a 3 times a day basis. Patients continued the oral medication on a 3 times a day basis on each day of radiotherapy.

Postoperative Nausea and Vomiting:

Surgical patients who received ondansetron 1 hour before the induction of general balanced anesthesia (barbiturate: thiopental, methohexital, or thiamylal; opioid: alfentanil, sufentanil, morphine, or fentanyl; nitrous oxide; neuromuscular blockade: succinylcholine/curare or gallamine and/or vecuronium, pancuronium, or atracurium; and supplemental isoflurane or enflurane) were evaluated in 2 double-blind studies (1 US study, 1 foreign) involving 865 patients. Ondansetron tablets (16 mg) were significantly more effective than placebo in preventing postoperative nausea and vomiting.

The study populations in all trials thus far consisted of women undergoing inpatient surgical procedures. No studies have been performed in males. No controlled clinical study comparing ondansetron tablets to ondansetron hydrochloride injection has been performed.

INDICATIONS AND USAGE

- Prevention of nausea and vomiting associated with highly emetogenic cancer chemotherapy, including cisplatin ≥50 mg/m^2.
- Prevention of nausea and vomiting associated with initial and repeat courses of moderately emetogenic cancer chemotherapy.
- Prevention of nausea and vomiting associated with radiotherapy in patients receiving either total body irradiation, single high-dose fraction to the abdomen, or daily fractions to the abdomen.
- Prevention of postoperative nausea and/or vomiting. As with other antiemetics, routine prophylaxis is not recommended for patients in whom there is little expectation that nausea and/or vomiting will occur postoperatively. In patients where nausea and/or vomiting must be avoided postoperatively, ondansetron tablets USP and ondansetron orally disintegrating tablets USP are recommended even where the incidence of postoperative nausea and/or vomiting is low.

CONTRAINDICATIONS

The concomitant use of apomorphine with ondansetron is contraindicated based on reports of profound hypotension and loss of consciousness when apomorphine was administered with ondansetron.

Ondansetron tablets and ondansetron orally disintegrating tablets are contraindicated for patients known to have hypersensitivity to the drug.

WARNINGS

Hypersensitivity reactions have been reported in patients who have exhibited hypersensitivity to other selective 5-HT3 receptor antagonists.

ECG changes including QT interval prolongation has been seen in patients receiving ondansetron. In addition, post-marketing cases of Torsade de Pointes have been reported in patients using ondansetron. Avoid ondansetron in patients with congenital long QT syndrome. ECG monitoring is recommended in patients with electrolyte abnormalities (e.g., hypokalemia or hypomagnesemia), congestive heart failure, bradyarrhythmias or patients taking other medicinal products that lead to QT prolongation.

PRECAUTIONS

General

Ondansetron is not a drug that stimulates gastric or intestinal peristalsis. It should not be used instead of nasogastric suction. The use of ondansetron in patients following abdominal surgery or in patients with chemotherapy-induced nausea and vomiting may mask a progressive ileus and/or gastric distension.

Information for Patients

Phenylketonurics:

Phenylketonuric patients should be informed that ondansetron orally disintegrating tablets contain phenylalanine (a component of aspartame). Each 4 mg and 8 mg orally disintegrating tablet contains 1.5 mg and 3 mg of phenylalanine, respectively.

Patients should be instructed not to remove ondansetron orally disintegrating tablets from the blister until just prior to dosing. The tablet should not be pushed through the foil. With dry hands, the blister backing should be peeled completely off the blister. The tablet should be gently removed and immediately placed on the tongue to dissolve and be swallowed with the saliva. Peelable illustrated stickers are affixed to the product carton that can be provided with the prescription to ensure proper use and handling of the product.

Drug Interactions

Ondansetron does not itself appear to induce or inhibit the cytochrome P-450 drug-metabolizing enzyme system of the liver (see CLINICAL PHARMACOLOGY, Pharmacokinetics). Because ondansetron is metabolized by hepatic cytochrome P-450 drug-metabolizing enzymes (CYP3A4, CYP2D6, CYP1A2), inducers or inhibitors of these enzymes may change the clearance and, hence, the half-life of ondansetron. On the basis of available data, no dosage adjustment is recommended for patients on these drugs.

Apomorphine: Based on reports of profound hypotension and loss of consciousness when apomorphine was administered with ondansetron, concomitant use of apomorphine with ondansetron is contraindicated (see CONTRAINDICATIONS).

Phenytoin, Carbamazepine, and Rifampicin: In patients treated with potent inducers of CYP3A4 (i.e., phenytoin, carbamazepine, and rifampicin), the clearance of ondansetron was significantly increased and ondansetron blood concentrations were decreased. However, on the basis of available data, no dosage adjustment for ondansetron is recommended for patients on these drugs.^1,3

Tramadol: Although no pharmacokinetic drug interaction between ondansetron and tramadol has been observed, data from 2 small studies indicate that ondansetron may be associated with an increase in patient controlled administration of tramadol.^4,5

Chemotherapy: Tumor response to chemotherapy in the P-388 mouse leukemia model is not affected by ondansetron. In humans, carmustine, etoposide, and cisplatin do not affect the pharmacokinetics of ondansetron.

In a crossover study in 76 pediatric patients, I.V. ondansetron did not increase blood levels of high-dose methotrexate.

Use in Surgical Patients: The coadministration of ondansetron had no effect on the pharmacokinetics and pharmacodynamics of temazepam.

Pregnancy

Teratogenic Effects

Pregnancy Category B. Reproduction studies have been performed in pregnant rats and rabbits at daily oral doses up to 15 and 30 mg/kg/day, respectively, and have revealed no evidence of impaired fertility or harm to the fetus due to ondansetron. There are, however, no adequate and well-controlled studies in pregnant women. Because animal reproduction studies are not always predictive of human response, this drug should be used during pregnancy only if clearly needed.

Nursing Mothers

Ondansetron is excreted in the breast milk of rats. It is not known whether ondansetron is excreted in human milk. Because many drugs are excreted in human milk, caution should be exercised when ondansetron is administered to a nursing woman.

Pediatric Use

Little information is available about dosage in pediatric patients 4 years of age or younger (see Error! Hyperlink reference not valid. and Error! Hyperlink reference not valid. sections for use in pediatric patients 4 to 18 years of age).

Geriatric Use

Of the total number of subjects enrolled in cancer chemotherapy-induced and postoperative nausea and vomiting in US- and foreign-controlled clinical trials, for which there were subgroup analyses, 938 were 65 years of age and over. No overall differences in safety or effectiveness were observed between these subjects and younger subjects, and other reported clinical experience has not identified differences in responses between the elderly and younger patients, but greater sensitivity of some older individuals cannot be ruled out. Dosage adjustment is not needed in patients over the age of 65 (see Error! Hyperlink reference not valid.).

ADVERSE REACTIONS

The following have been reported as adverse events in clinical trials of patients treated with ondansetron, the active ingredient of ondansetron tablets and ondansetron orally disintegrating tablets. A causal relationship to therapy with ondansetron tablets and ondansetron orally disintegrating tablets has been unclear in many cases.

Chemotherapy-Induced Nausea and Vomiting:

The adverse events in Table 5 have been reported in ≥5% of adult patients receiving a single 24-mg ondansetron tablet in 2 trials. These patients were receiving concurrent highly emetogenic cisplatin-based chemotherapy regimens (cisplatin dose ≥50 mg/m^2).

Table 1. Principal Adverse Events in US Trials: Single Day Therapy With 24-mg Ondansetron Tablets (Highly Emetogenic Chemotherapy)
Event | Ondansetron 24 mg q.d.; n = 300 | Ondansetron 8 mg b.i.d.; n = 124 | Ondansetron 32 mg q.d.; n = 117
Headache | 33 (11%) | 16 (13%) | 17 (15%)
Diarrhea | 13 (4%) | 9 (7%) | 3 (3%)

The adverse events in Table 6 have been reported in ≥5% of adults receiving either 8 mg of ondansetron tablets 2 or 3 times a day for 3 days or placebo in 4 trials. These patients were receiving concurrent moderately emetogenic chemotherapy, primarily cyclophosphamide-based regimens.

Table 6. Principal Adverse Events in US Trials: 3 Days of Therapy With 8-mg Ondansetron Tablets (Moderately Emetogenic Chemotherapy)

Event | Ondansetron 8 mg b.i.d.; n = 242 | Ondansetron 8 mg t.i.d.; n = 415 | Placebo; n = 262
Headache | 58 (24%) | 113 (27%) | 34 (13%)
Malaise/fatigue | 32 (13%) | 37 (9%) | 6 (2%)
Constipation | 22 (9%) | 26 (6%) | 1 (<1%)
Diarrhea | 15 (6%) | 16 (4%) | 10 (4%)
Dizziness | 13 (5%) | 18 (4%) | 12 (5%)

Central Nervous System:

There have been rare reports consistent with, but not diagnostic of, extrapyramidal reactions in patients receiving ondansetron.

Hepatic:

In 723 patients receiving cyclophosphamide-based chemotherapy in US clinical trials, AST and/or ALT values have been reported to exceed twice the upper limit of normal in approximately 1% to 2% of patients receiving ondansetron tablets. The increases were transient and did not appear to be related to dose or duration of therapy. On repeat exposure, similar transient elevations in transaminase values occurred in some courses, but symptomatic hepatic disease did not occur. The role of cancer chemotherapy in these biochemical changes cannot be clearly determined.

There have been reports of liver failure and death in patients with cancer receiving concurrent medications including potentially hepatotoxic cytotoxic chemotherapy and antibiotics. The etiology of the liver failure is unclear.

Integumentary:

Rash has occurred in approximately 1% of patients receiving ondansetron.

Other:

Rare cases of anaphylaxis, bronchospasm, tachycardia, angina (chest pain), hypokalemia, electrocardiographic alterations, vascular occlusive events, and grand mal seizures have been reported. Except for bronchospasm and anaphylaxis, the relationship to ondansetron was unclear.

Radiation-Induced Nausea and Vomiting:

The adverse events reported in patients receiving ondansetron tablets and concurrent radiotherapy were similar to those reported in patients receiving ondansetron tablets and concurrent chemotherapy. The most frequently reported adverse events were headache, constipation, and diarrhea.

Postoperative Nausea and Vomiting:

The adverse events in Table 7 have been reported in ≥5% of patients receiving ondansetron tablets at a dosage of 16 mg orally in clinical trials. With the exception of headache, rates of these events were not significantly different in the ondansetron and placebo groups. These patients were receiving multiple concomitant perioperative and postoperative medications.

Table 7. Frequency of Adverse Events From Controlled Studies With Ondansetron Tablets (Postoperative Nausea and Vomiting)

Adverse Event | Ondansetron 16 mg (n = 550) | Placebo (n = 531)
Wound problem | 152 (28%) | 162 (31%)
Drowsiness/sedation | 112 (20%) | 122 (23%)
Headache | 49 (9%) | 27 (5%)
Hypoxia | 49 (9%) | 35 (7%)
Pyrexia | 45 (8%) | 34 (6%)
Dizziness | 36 (7%) | 34 (6%)
Gynecological disorder | 36 (7%) | 33 (6%)
Anxiety/agitation | 33 (6%) | 29 (5%)
Bradycardia | 32 (6%) | 30 (6%)
Shiver(s) | 28 (5%) | 30 (6%)
Urinary retention | 28 (5%) | 18 (3%)
Hypotension | 27 (5%) | 32 (6%)
Pruritus | 27 (5%) | 20 (4%)

Preliminary observations in a small number of subjects suggest a higher incidence of headache when ondansetron orally disintegrating tablets are taken with water, when compared to without water.

Observed During Clinical Practice:

In addition to adverse events reported from clinical trials, the following events have been identified during post-approval use of oral formulations of ondansetron. Because they are reported voluntarily from a population of unknown size, estimates of frequency cannot be made. The events have been chosen for inclusion due to a combination of their seriousness, frequency of reporting, or potential causal connection to ondansetron.

Cardiovascular: Rarely and predominantly with intravenous ondansetron, transient ECG changes including QT interval prolongation have been reported.

General: Flushing. Rare cases of hypersensitivity reactions, sometimes severe (e.g., anaphylaxis/anaphylactoid reactions, angioedema, bronchospasm, shortness of breath, hypotension, laryngeal edema, stridor) have also been reported. Laryngospasm, shock, and cardiopulmonary arrest have occurred during allergic reactions in patients receiving injectable ondansetron.

Hepatobiliary: Liver enzyme abnormalities

Lower Respiratory: Hiccups

Neurology: Oculogyric crisis, appearing alone, as well as with other dystonic reactions

Skin: Urticaria, Stevens-Johnson syndrome, and toxic epidermal necrolysis.

Special Senses: Eye Disorders:Cases of transient blindness, predominantly during intravenous administration, have been reported. These cases of transient blindness were reported to resolve within a few minutes up to 48 hours.

DRUG ABUSE AND DEPENDENCE

Animal studies have shown that ondansetron is not discriminated as a benzodiazepine nor does it substitute for benzodiazepines in direct addiction studies.

OVERDOSAGE

There is no specific antidote for ondansetron overdose. Patients should be managed with appropriate supportive therapy. Individual intravenous doses as large as 150 mg and total daily intravenous doses as large as 252 mg have been inadvertently administered without significant adverse events. These doses are more than 10 times the recommended daily dose.

In addition to the adverse events listed above, the following events have been described in the setting of ondansetron overdose: “Sudden blindness” (amaurosis) of 2 to 3 minutes’ duration plus severe constipation occurred in 1 patient that was administered 72 mg of ondansetron intravenously as a single dose. Hypotension (and faintness) occurred in a patient that took 48 mg of ondansetron tablets. Following infusion of 32 mg over only a 4-minute period, a vasovagal episode with transient second-degree heart block was observed. In all instances, the events resolved completely.

DOSAGE AND ADMINISTRATION

Instructions for Use/Handling Ondansetron Orally Disintegrating Tablets USP:

Do not attempt to push ondansetron orally disintegrating tablets USP through the foil backing. With dry hands, PEEL BACK the foil backing of 1 blister and GENTLY remove the tablet. IMMEDIATELY place the ondansetron orally disintegrating tablet USP on top of the tongue where it will dissolve in seconds, then swallow with saliva. Administration with liquid is not necessary.

Prevention of Nausea and Vomiting Associated With Highly Emetogenic Cancer Chemotherapy:

The recommended adult oral dosage of ondansetron is 24 mg given as three 8-mg tablets administered 30 minutes before the start of single-day highly emetogenic chemotherapy, including cisplatin ≥50 mg/m^2. Multiday, single-dose administration of a 24 mg dosage has not been studied.

Pediatric Use:

There is no experience with the use of a 24 mg dosage in pediatric patients.

Geriatric Use:

The dosage recommendation is the same as for the general population.

Prevention of Nausea and Vomiting Associated With Moderately Emetogenic Cancer Chemotherapy:

The recommended adult oral dosage is one 8-mg ondansetron tablet USP or one 8-mg ondansetron orally disintegrating tablet USP given twice a day. The first dose should be administered 30 minutes before the start of emetogenic chemotherapy, with a subsequent dose 8 hours after the first dose. One 8-mg ondansetron tablet USP or one 8-mg ondansetron orally disintegrating tablet USP should be administered twice a day (every 12 hours) for 1 to 2 days after completion of chemotherapy.

Pediatric Use:

For pediatric patients 12 years of age and older, the dosage is the same as for adults. For pediatric patients 4 through 11 years of age, the dosage is one 4-mg ondansetron tablet USP or one 4-mg ondansetron orally disintegrating tablet USP given 3 times a day. The first dose should be administered 30 minutes before the start of emetogenic chemotherapy, with subsequent doses 4 and 8 hours after the first dose. One 4-mg ondansetron tablet USP or one 4-mg ondansetron orally disintegrating tablet USP should be administered 3 times a day (every 8 hours) for 1 to 2 days after completion of chemotherapy.

Geriatric Use:

The dosage is the same as for the general population.

Prevention of Nausea and Vomiting Associated With Radiotherapy, Either Total Body Irradiation, or Single High-Dose Fraction or Daily Fractions to the Abdomen:

The recommended oral dosage is one 8-mg ondansetron tablet USP or one 8-mg ondansetron orally disintegrating tablet USP given 3 times a day.

For total body irradiation, one 8-mg ondansetron tablet USP or one 8-mg ondansetron orally disintegrating tablet USP should be administered 1 to 2 hours before each fraction of radiotherapy administered each day.

For single high-dose fraction radiotherapy to the abdomen, one 8-mg ondansetron tablet USP or one 8-mg ondansetron orally disintegrating tablet USP should be administered 1 to 2 hours before radiotherapy, with subsequent doses every 8 hours after the first dose for 1 to 2 days after completion of radiotherapy.

For daily fractionated radiotherapy to the abdomen, one 8-mg ondansetron tablet USP or one 8-mg ondansetron orally disintegrating tablet USP should be administered 1 to 2 hours before radiotherapy, with subsequent doses every 8 hours after the first dose for each day radiotherapy is given.

Pediatric Use:

There is no experience with the use of ondansetron tablets USP or ondansetron orally disintegrating tablets USP in the prevention of postoperative nausea and vomiting in pediatric patients.

Geriatric Use:

The dosage recommendation is the same as for the general population.

Postoperative Nausea and Vomiting:

The recommended dosage is 16 mg given as two 8-mg ondansetron tablets USP or two 8-mg ondansetron orally disintegrating tablets USP 1 hour before induction of anesthesia.

Pediatric Use:

There is no experience with the use of ondansetron tablets USP or ondansetron orally disintegrating tablets USP in the prevention of postoperative nausea and vomiting in pediatric patients.

Geriatric Use:

The dosage is the same as for the general population.

Dosage Adjustment for Patients With Impaired Renal Function:

The dosage recommendation is the same as for the general population. There is no experience beyond first-day administration of ondansetron.

Dosage Adjustment for Patients With Impaired Hepatic Function:

In patients with severe hepatic impairment (Child-Pugh^2 score of 10 or greater), clearance is reduced and apparent volume of distribution is increased with a resultant increase in plasma half-life. In such patients, a total daily dose of 8 mg should not be exceeded.

HOW SUPPLIED

Ondansetron orally disintegrating tablets USP, 4 mg (as 4 mg ondansetron base) are white, circular, flat faced, uncoated tablets with ‘G’ engraved on one side and ‘4’ on the other side in:

Unit dose packs of 4 tablets (NDC 63187-256-04)

Unit dose packs of 5 tablets (NDC 63187-256-05)

Unit dose packs of 6 tablets (NDC 63187-256-06)

Unit dose packs of 10 tablets (NDC 63187-256-10)

Unit dose packs of 12 tablets (NDC 63187-256-12)

Unit dose packs of 15 tablets (NDC 63187-256-15)

Carton of 20 tablets (contains 2 cards of 10 unit of use blisters) NDC 63187-256-20

Carton of 30 tablets (contains 3 cards of 10 unit of use blisters) NDC 63187-256-30

Ondansetron orally disintegrating tablets USP, 8 mg (as 8 mg ondansetron base) are white, circular, flat faced, uncoated tablets with ‘G’ engraved on one side and ‘8’ on the other side in:

Unit dose packs of 10 tablets (NDC 63187-199-10)

Unit dose packs of 20 tablets (NDC 63187-199-20)

Unit dose packs of 30 tablets (NDC 63187-199-30)

Store at 20° to 25°C (68° to 77°F) [See USP Controlled Room Temperature].

REFERENCES

- Britto MR, Hussey EK, Mydlow P, et al. Effect of enzyme inducers on ondansetron (OND) metabolism in humans. Clin Pharmacol Ther. 1997;61:228.
- Pugh RNH, Murray-Lyon IM, Dawson JL, Pietroni MC, Williams R. Transection of the oesophagus for bleeding oesophageal varices. Brit J Surg. 1973;60:646-649.
- Villikka K, Kivisto KT, Neuvonen PJ. The effect of rifampin on the pharmacokinetics of oral and intravenous ondansetron. Clin Pharmacol Ther. 1999;65:377-381.
- De Witte JL, Schoenmaekers B, Sessler DI, et al. Anesth Analg. 2001;92:1319-1321.
- Arcioni R, della Rocca M, Romanò R, et al. Anesth Analg. 2002;94:1553-1557.

Manufactured by:

Glenmark Generics Ltd.
Colvale-Bardez, Goa 403 513, India

Manufactured for:

Glenmark Generics Inc., USA
Mahwah, NJ 07430

Questions? 1 (888)721-7115

www.glenmarkgenerics.com

Relabeled by:

Proficient Rx LP
Thousand Oaks, CA 91320

January 2014